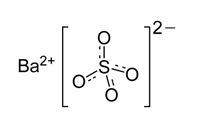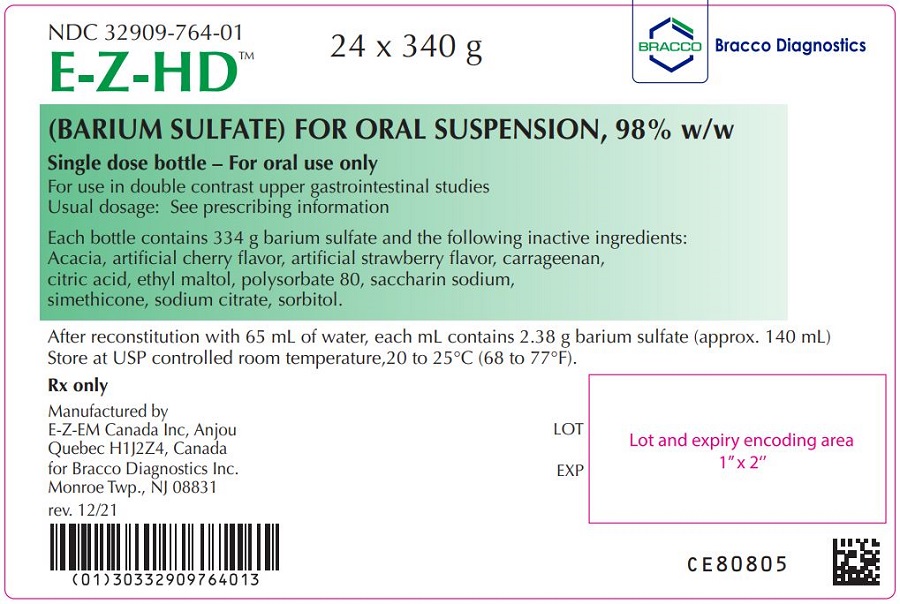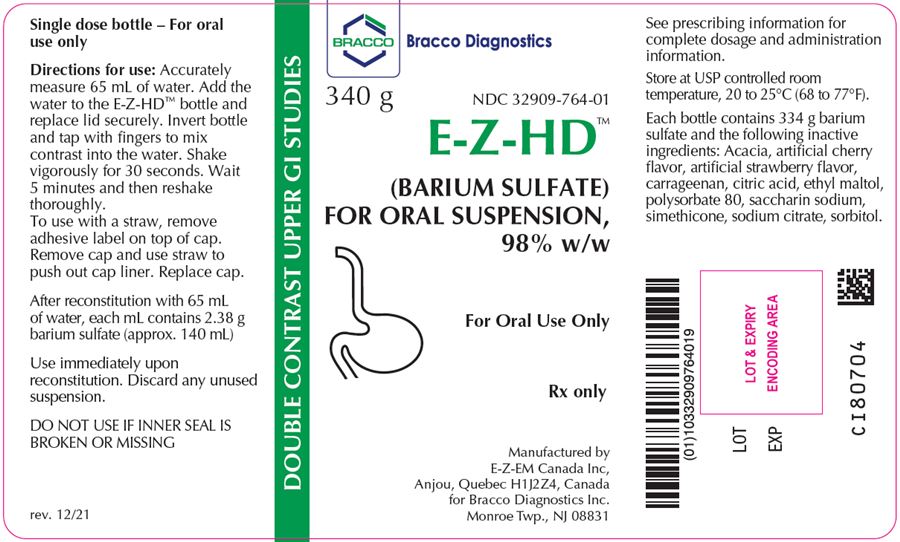 DRUG LABEL: E-Z-HD
NDC: 32909-764 | Form: POWDER, FOR SUSPENSION
Manufacturer: E-Z-EM Canada Inc
Category: prescription | Type: HUMAN PRESCRIPTION DRUG LABEL
Date: 20221104

ACTIVE INGREDIENTS: Barium Sulfate 980 mg/1 g
INACTIVE INGREDIENTS: acacia; anhydrous citric acid; dimethicone 1000; ethyl maltol; polysorbate 80; saccharin sodium; silicon dioxide; trisodium citrate dihydrate; sorbitol; carrageenan sodium

HIGHLIGHTS OF PRESCRIBING INFORMATION

These highlights do not include all the information needed to use E-Z-HD safely and effectively. See full prescribing information for E-Z-HD.
E-Z-HD (barium sulfate) for oral suspension,
Initial U.S. Approval: 2016

RECENT MAJOR CHANGES

Warnings and Precautions (5.6) | 2/2017

1 INDICATIONS AND USAGE

E-Z-HD, a radiographic contrast agent, is indicated for use in double-contrast radiographic examinations of the esophagus, stomach and duodenum to visualize the gastrointestinal (GI) tract in patients 12 years and older (1)

2 DOSAGE AND ADMINISTRATION

- Recommended reconstituted oral dose for adults and pediatric patients 12 years and older is between 65 mL to 135 mL (155 to 321 grams of barium sulfate, respectively) (2.1)
- Must reconstitute supplied powder with water prior to use. See Full Prescribing Information for reconstitution instructions (2.2)

3 DOSAGE FORMS AND STRENGTHS

For oral suspension: 334 grams of barium sulfate (98 % w/w) in a single-dose bottle for reconstitution(3)

4 CONTRAINDICATIONS

- Known or suspected perforation of the GI tract (4)
- Conditions associated to high risk of aspiration (4)
- Conditions associated to high risk of GI perforation (4)
- Known hypersensitivity to barium sulfate or any of the excipients of E-Z-HD (4)

5 WARNINGS AND PRECAUTIONS

- Emergency equipment and trained personnel should be immediately available for treatment of a serious hypersensitivity reaction (5.1)
- Intra-abdominal leakage: Caution is recommended in patient conditions like GI fistula, ulcer, inflammatory bowel disease, appendicitis or diverticulitis, severe stenosis or obstructing lesions of the GI tract (5.2)
- Patients should maintain adequate hydration in days following a barium sulfate procedure to avoid obstruction or impaction caused by baroliths (5.3)
- Aspiration: Caution is recommended in patients with history of food aspiration and in patients with known swallowing disorders (5.4)
- E-Z-HD is not intended for pediatric use from birth through 11 years of age (8.4)

6 ADVERSE REACTIONS

Common adverse reactions include nausea, vomiting, diarrhea and abdominal cramping (6)

To report SUSPECTED ADVERSE REACTIONS, contact Bracco Diagnostics Inc at 1-800-257-5181 or FDA at 1-800-FDA-1088 or www.fda.gov/medwatch

FULL PRESCRIBING INFORMATION

1 INDICATIONS AND USAGE

E-Z-HD is indicated for use in double-contrast radiographic examinations of the esophagus, stomach and duodenum to help visualize the gastrointestinal (GI) tract in patients 12 years and older.

2 DOSAGE AND ADMINISTRATION

2.1 Recommended Dosage

The recommended dose of reconstituted E-Z-HD for adults and pediatric patients 12 years and olderis between 65 and 135 mL given orally (155 to 321 grams of barium sulfate, respectively). Volumes closer to 65 mL are recommended for the examination of the esophagus and volumes up to 135 mL are recommended for examination of the entire upper GI tract.

2.2 Instructions for Reconstitution

The E-Z-HD powder must be reconstituted prior to administration by a healthcare provider according to the following instructions:

- Accurately measure 65 mL of water and add this water to the bottle containing the supplied E-Z-HD powder
- Replace cap securely on bottle and shake vigorously for 30 seconds
- Wait 5 minutes and re-shake bottle thoroughly. Reconstitution yields approximately 140 mL of E-Z-HD for oral suspension containing 2.38 grams of barium sulfate per mL

2.3 Administration Instructions

- Administer the reconstituted E-Z-HD for oral suspension immediately upon reconstitution
- To use with a straw, remove the adhesive label from top of the cap. Remove cap and use straw to push out cap liner. Replace cap
- Discard any unused suspension
- Advise patients to hydrate following the barium sulfate procedure

3 DOSAGE FORMS AND STRENGTHS

For oral suspension: 334 grams of barium sulfate supplied as a fine, white to lightly colored powder (98 % w/w) in a single-dose HDPE plastic bottle for reconstitution. The suspension is 238% w/v when reconstituted and should be homogeneous and white to lightly colored.

4 CONTRAINDICATIONS

E-Z-HD is contraindicated in patients:

- Known or suspected perforation of the GI tract
- Known obstruction of the GI tract
- At high risk of GI perforation such as those with a recent prior GI perforation, acute GI hemorrhage or ischemia, toxic megacolon, severe ileus, post GI surgery or biopsy, acute GI injury or burn, or recent radiotherapy to the pelvis
- At high risk of aspiration such as those with prior aspiration, tracheo-esophageal fistula, or obtundation
- With known severe hypersensitivity to barium sulfate or any of the E-Z-HD excipients

5 WARNINGS AND PRECAUTIONS

5.1 Hypersensitivity Reactions

Barium sulfate preparations contain a number of excipients, including natural and artificial flavors and may induce serious hypersensitivity reactions. The manifestations include hypotension, bronchospasm and other respiratory impairments, dermal reactions including rashes, urticaria, and itching. A history of bronchial asthma, atopy, or a previous reaction to a contrast agent may increase the risk for hypersensitivity reactions. Emergency equipment and trained personnel should be immediately available for treatment of a hypersensitivity reaction.

5.2 Intra-abdominal Barium Leakage

The use of E-Z-HD is contraindicated in patients at high risk of perforation of the GI tract [see Contraindications (4)]. Administration of E-Z-HD may result in leakage of barium from the GI tract in the presence of conditions such as carcinomas, GI fistula, inflammatory bowel disease, gastric or duodenal ulcer, appendicitis, or diverticulitis, and in patients with a severe stenosis at any level of the GI tract, especially if it is distal to the stomach. The barium leakage has been associated with peritonitis and granuloma formation.

5.3 Delayed Gastrointestinal Transit and Obstruction

Orally administered barium sulfate may accumulate proximal to a constricting lesion of the colon, causing obstruction or impaction with development of baroliths (inspissated barium associated with feces) and may lead to abdominal pain, appendicitis, bowel obstruction, or rarely perforation. Patients with the following conditions are at higher risk for developing obstruction or baroliths: severe stenosis at any level of the GI tract, impaired GI motility, electrolyte imbalance, dehydration, on a low residue diet, taking medications that delay GI motility, constipation, pediatric patients with cystic fibrosis or Hirschsprung disease, and the elderly [see Use in Specific Populations (8.4, 8.5)]. To reduce the risk of delayed GI transit and obstruction, patients should maintain adequate hydration during and in the days following a barium sulfate procedure. Consider the administration of laxatives.

5.4 Aspiration Pneumonitis

The use of E-Z-HD is contraindicated in patients at high risk of aspiration [see Contraindications (4)]. Oral administration of barium is associated with aspiration pneumonitis, especially in patients with a history of food aspiration or with compromised swallowing mechanism. Vomiting following oral administration of barium sulfate may lead to aspiration pneumonitis. In patients at risk for aspiration, begin the procedure with a small ingested volume of E-Z-HD. Discontinue administration of E-Z-HD immediately if aspiration is suspected.

5.5 Systemic Embolization

Barium sulfate products may occasionally intravasate into the venous drainage of the large bowel and enter the circulation as a "barium embolus" leading to potentially fatal complications which include systemic and pulmonary embolism, disseminated intravascular coagulation, septicemia and prolonged severe hypotension. Although this complication is exceedingly uncommon after oral administration of a barium sulfate suspension, monitor patients for potential intravasation when administering barium sulfate.

5.6 Risk with Hereditary Fructose Intolerance

E-Z-HD contains sorbitol which may cause severe reactions if ingested by patients with hereditary fructose intolerance, such as: vomiting, hypoglycemia, jaundice, hemorrhage, hepatomegaly, hyperuricemia, and kidney failure. Before administration of E-Z-HD assess patients for a history of hereditary fructose intolerance and avoid use in these patients.

6 ADVERSE REACTIONS

The following adverse reactions have been identified from spontaneous reporting or clinical studies of barium sulfate administered orally. Because the reactions are reported voluntarily from a population of uncertain size, it is not always possible to reliably estimate their frequency or to establish a causal relationship to drug exposure

- Nausea, vomiting, diarrhea and abdominal cramping
- Serious adverse reactions and fatalities include aspiration pneumonitis, barium sulfate impaction, intestinal perforation with consequent peritonitis and granuloma formation, vasovagal and syncopal episodes

8 USE IN SPECIFIC POPULATIONS

8.1 Pregnancy

Risk Summary

E-Z-HD is not absorbed systemically following oral administration, and maternal use is not expected to result in fetal exposure to the drug.

8.2 Lactation

Risk Summary
E-Z-HD is not absorbed systemically by the mother following oral administration, and breastfeeding is not expected to result in exposure of the infant to E-Z-HD.

8.4 Pediatric Use

Double-contrast radiographic examinations of the esophagus, stomach and duodenum may be used in pediatric patients 12 years and older.

E-Z-HD is contraindicated in pediatric patients with tracheo-esophageal fistula. [see Contraindications (4)]. Pediatric patients with a history of asthma or food allergies may be at increased risk for development of hypersensitivity reactions [see Warnings and Precautions (5.1)]. Pediatric patients with cystic fibrosis or Hirschsprung disease should be monitored for bowel obstruction after use [see Warnings and Precautions (5.3)]

8.5 Geriatric Use

Clinical studies of E-Z-HD did not include sufficient numbers of subjects aged 65 and over to determine whether they respond differently from younger subjects. Other reported clinical experience has not identified differences in responses between the elderly and younger patients. In general, dose selection for an elderly patient should be cautious, usually starting at the low end of the dosing range, reflecting the greater frequency of decreased hepatic, renal, or cardiac function, and of concomitant disease or other drug therapy.

11 DESCRIPTION

E-Z-HD (barium sulfate) is a radiographic contrast agent that is supplied as a fine, white to lightly colored powder for suspension (98 % w/w) for oral administration. The active ingredient barium sulfate is designated chemically as BaSO4 with a molecular weight of 233.43 g/mol, a density of 4.5 g/cm^3, and the following chemical structure:

E-Z-HD contains excipients including: acacia, artificial cherry flavor, artificial strawberry flavor, carrageenan, citric acid, ethyl maltol, polysorbate 80, saccharin sodium, simethicone, sodium citrate, and sorbitol.

12 CLINICAL PHARMACOLOGY

12.1 Mechanism of Action

Due to its high atomic number, barium (the active ingredient in E-Z-HD) is opaque to x-rays and therefore acts as a positive contrast agent for radiographic studies.

12.3 Pharmacokinetics

Under physiological conditions, barium sulfate passes through the GI tract in an unchanged form and is absorbed only in pharmacologically insignificant amounts.

13 NONCLINICAL TOXICOLOGY

13.1 Carcinogenesis, Mutagenesis, Impairment of Fertility

No animal studies have been performed to evaluate the carcinogenic potential of barium sulfate or potential effects on fertility.

16 HOW SUPPLIED/STORAGE AND HANDLING

16.1 How Supplied
E-Z-HD (barium sulfate) for suspension, is supplied as a fine, white to lightly colored powder (98 % w/w) in a single-dose HDPE plastic bottle containing 334 grams of barium sulfate.

Provided as: 24 bottles per pack (NDC 32909-764-01)

16.2 Storage and Handling
Store at USP controlled room temperature, 20 to 25°C (68 to 77° F).

17 PATIENT COUNSELING INFORMATION

After administration advise patients to:

- Maintain adequate hydration
- Seek medical attention for worsening of constipation or slow gastrointestinal passage
- Seek medical attention for any delayed onset of hypersensitivity: rash, urticaria, or respiratory difficulty

Manufactured by
EZEM Canada Inc
Anjou (Quebec) Canada H1J 2Z4
For
Bracco Diagnostics Inc.
Monroe Township, NJ 08831

CL80608

Revised December 2021

PACKAGE LABEL

EZ-HD Labels
NDC: 32909-764-01